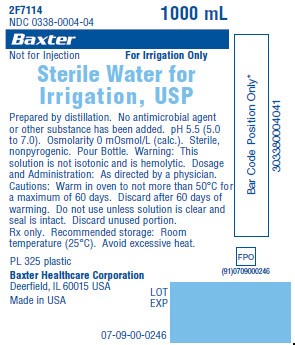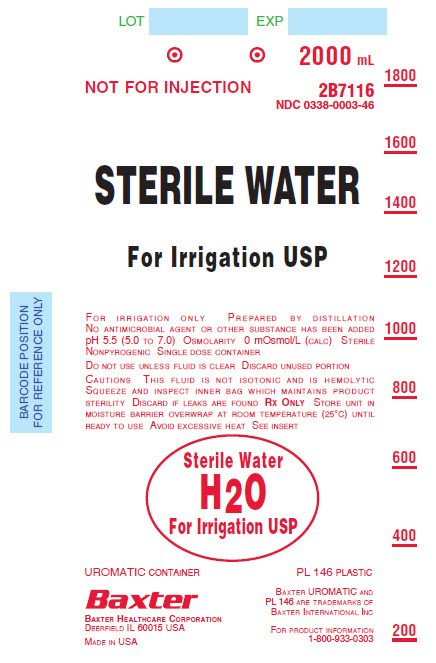 DRUG LABEL: Sterile Water
NDC: 0338-0003 | Form: IRRIGANT
Manufacturer: Baxter Healthcare Corporation
Category: prescription | Type: HUMAN PRESCRIPTION DRUG LABEL
Date: 20171017

ACTIVE INGREDIENTS: WATER 100 mL/100 mL

HIGHLIGHTS OF PRESCRIBING INFORMATION

These highlights do not include all the information needed to use STERILE WATER FOR IRRIGATION safely and effectively. See full prescribing information for STERILE WATER FOR IRRIGATION.
STERILE WATER FOR IRRIGATION
Initial U.S. Approval: 1974

1 INDICATIONS AND USAGE

Sterile Water for Irrigation is indicated for use as an irrigant. (1)

2 DOSAGE AND ADMINISTRATION

- For Irrigation only. Not for injection or infusion by usual parenteral routes. (2.1, 5.1)
- The volume and/or rate of irrigation depend on the type of the procedure and the capacity or the surface area of the structure to be irrigated. (2.2)
- For preparation and administration instructions see the full prescribing information. (2.1, 2.3)

3 DOSAGE FORMS AND STRENGTHS

- 250, 500, 1000, and 1500 mL sterile water for irrigation in a single-dose plastic pour bottle. (3)
- 1000, 2000 and 3000 mL sterile water for irrigation in a single-dose flexible plastic container. (3)

4 CONTRAINDICATIONS

- None. (4)

5 WARNINGS AND PRECAUTIONS

- Hypotonicity: Administration by parenteral routes can result in serious adverse reactions. For irrigation use only. (5.1)
- Excessive Water Absorption: May result in hyponatremia, hypoosmolality and fluid overload. Monitor patients for absorption of clinically relevant amounts of fluid during and after the procedure. Additional monitoring is recommended for patients at increased risk of developing complications of fluid overload syndrome (e.g., patients with renal or cardiac impairment) or hyponatremic encephalopathy (e.g., pediatric patients; women, in particular premenopausal women; patients with hypoxemia; and patients with central nervous system disease). Avoid use in procedures that require longer irrigation times or an irrigation fluid pressure that promotes absorption. (5.2, 8.4)
- Use with Electrosurgery/Cautery: Ensure compatibility with equipment used with electrosurgery or cautery. (5.2)

6 ADVERSE REACTIONS

Most common adverse reactions are: hyponatremia, fluid overload, fluid absorption, electrolyte imbalance. (6)

To report SUSPECTED ADVERSE REACTIONS, contact Baxter Healthcare Corporation at 1-866-888-2472 or FDA at 1-800-FDA-1088 or www.fda.gov/medwatch.

FULL PRESCRIBING INFORMATION

1 INDICATIONS AND USAGE

Sterile Water for Irrigation is indicated for use as an irrigant.

2 DOSAGE AND ADMINISTRATION

2.1 Important Administration Instructions

- For irrigation only. Not for intravenous injection.
- Sterile Water for Irrigation is hypotonic with an osmolarity of zero mOsmol/L. It is intended for use as an irrigation fluid and not for intravenous administration or administration by other, parenteral routes (e.g., subcutaneous or intramuscular) [see Warnings and Precautions (5.1)].
- Sterile Water for Irrigation is not potable water and is not intended for oral administration.
- Sterile Water for Irrigation that has been warmed must not be returned to storage.

2.2 Recommended Dosage

The volume and/or rate of irrigation depend on the type of the procedure and the capacity or the surface area of the structure to be irrigated.

2.3 Preparation and Administration Instructions

For single-dose only. Sterile Water for Irrigation is available in a flexible plastic container and a plastic pour bottle. Use the contents of the opened container immediately to minimize the potential for bacterial growth and pyrogen formation. Discard the unused contents of opened containers, as Sterile Water for Irrigation contains no antimicrobial preservative.

Adding Medications to Either the Flexible Plastic Container or the Plastic Pour Bottle

- Use aseptic technique when making additions to Sterile Water for Irrigation.
- Additives may be incompatible with Sterile Water for Irrigation.
- The compatibility of additives with Sterile Water for Irrigation must be assessed. Before introducing additives, check for a possible color change and/or the appearance of precipitates, insoluble complexes, or crystals.
- Before adding a substance or medication, verify that it is soluble and/or stable in water and that the pH range of Sterile Water for Irrigation is appropriate.
- Additives known or determined to be incompatible should not be used.
- Mix thoroughly after additives have been introduced.
- Use immediately.

Administration Instructions for Irrigation by Gravity Using the Flexible Plastic Container

1. Use aseptic technique.
2. Tear overwrap down side at slit and remove solution container. Visually inspect the container. If the outlet port protector is damaged, detached, or not present, discard container as solution path sterility may be impaired. Some opacity of the plastic due to moisture absorption during the sterilization process may be observed. This is normal and does not affect the solution quality or safety. The opacity will diminish gradually. Check for minute leaks by squeezing the container firmly. If leaks are found, discard solution as sterility may be impaired.
3. Suspend container using hanger hole.
4. Remove plastic protector from outlet port at bottom of container.
5. Attach irrigation set. Refer to complete directions accompanying set.

Warming

If desired, warm the flexible plastic container in overwrap to near body temperature in a water bath or fluid warmer heated to not more than 45°C.

Microwave heating of irrigation fluids is not recommended.

Administration Using the Plastic Pour Bottle

1. Inspect Sterile Water for Irrigation visually for particulate matter and discoloration prior to use. Discard if the fluid is not clear or the seal is broken.
2. Use aseptic technique
3. Remove the plastic shrink band by tearing along the perforation line and unscrew the bottle cap.
4. Prevent contact of the fluid with the external surface of the container (including the thread for the bottle cap of the plastic pour bottle).

Warming

If desired, warm the plastic pour bottle in a fluid warmer to not more than 50°C for a maximum of 60 days. Discard after 60 days of warming.

Microwave heating of irrigation fluids is not recommended.

3 DOSAGE FORMS AND STRENGTHS

Irrigation:

- 250, 500, 1000, and 1500 mL sterile water for irrigation in a single-dose plastic pour bottle
- 1000, 2000 and 3000 mL sterile water for irrigation in a single-dose flexible plastic container

4 CONTRAINDICATIONS

None.

5 WARNINGS AND PRECAUTIONS

5.1 Hypotonicity

Sterile Water for Irrigation is hypotonic with an osmolarity of zero mOsmol/L. It is intended for use as irrigation fluid and not for intravenous administration or administration by other, usual parenteral routes, such as intravascular administration in general, subcutaneous administration, or intramuscular administration.

Serious adverse reactions, including cerebral or pulmonary edema, massive hemolysis, and acute renal failure can result from the hypotonicity of Sterile Water for Irrigation [see Warnings and Precautions (5.2)].

5.2 Excessive Water Absorption

Due to the hypotonicity, absorption of Sterile Water for Irrigation can result in serious adverse reactions of hyponatremia, hypoosmolality and fluid overload, resulting in fatality or permanent morbidity. Complications include cerebral edema, encephalopathy, pulmonary edema, massive hemolysis, rhabdomyolysis, renal failure, and hyperkalemia [see Adverse Reactions (6)]. In addition, excessive volume or pressure of the irrigation fluid may also cause undue distension of body cavities and may cause tissue disruption (e.g., tears or perforation). These complications can manifest after irrigation has ended and immediate intervention may be required.

Monitor patients closely for absorption of clinically relevant amounts of fluid during and for an appropriate period after the procedure. If absorption occurs, discontinue Sterile Water for Irrigation.

Additional close monitoring during and/or after the procedure is recommended for patients at increased risk for developing complications related to hypotonicity, such as:

- fluid overload syndrome, including patients with severe renal impairment, impaired cardiac function, or other clinical conditions associated with edematous states.
- hyponatremic encephalopathy, including pediatric patients; women, in particular premenopausal women; patients with hypoxemia; and patients with underlying central nervous system disease.

Avoid use of Sterile Water for Irrigation in patients with wounds where significant absorption may occur, such as procedures that require irrigation over a longer period of time or an irrigation fluid pressure that promotes absorption (e.g., transurethral resection of prostate). Sterile Water for Irrigation should only be used by clinicians familiar with the treatment of possible complications.

5.3 Use with Electrosurgery/Cautery

In contrast to other irrigation fluids containing electrolytes, Sterile Water for Irrigation is non-conductive. Therefore, when choosing the distension solution/fluid used with electrosurgery or cautery, ensure compatibility with the equipment.

6 ADVERSE REACTIONS

The following adverse reactions have been identified during post approval use of Sterile Water for Irrigation. Because these reactions are reported voluntarily from a population of uncertain size, it is not always possible to reliably estimate their frequency or establish a causal relationship to drug exposure.

Metabolism and Nutrition disorders: Hyponatremia, fluid overload, fluid absorption, electrolyte imbalance
Nervous System Disorders: Cerebral edema
General Disorders and Administration Site Conditions: Burning sensation (with irrigation of eyes and skin wounds)
Musculoskeletal and Connective Tissue Disorders: Rhabdomyolysis (myoglobinuria)
Renal and Urinary Disorders: Renal failure

Other Adverse reactions which may occur in association with absorption of water for irrigation include:

Blood and Lymphatic System Disorders: Hemolysis (hemoglobinemia, hemoglobinuria)
Metabolism and Nutrition Disorders: Hypervolemia, hypoosmolality, hyperkalemia, acid/base balance disorder
Nervous System Disorders: Encephalopathy (seizure, loss of vision, lethargy, disorientation, irritability, vomiting, nausea, headache)
Cardiac Disorders: Cardiac arrest, cardiac failure, bradycardia, electrocardiogram abnormal
Vascular Disorders: Hypertension, postoperative hypotension
Respiratory, Thoracic and Mediastinal Disorders: Respiratory arrest, respiratory failure, pulmonary edema

8 USE IN SPECIFIC POPULATIONS

8.1 Pregnancy

Risk Summary

Appropriate administration of Sterile Water for Irrigation is not expected to cause adverse developmental outcomes. There are no available data on Sterile Water for Irrigation use in pregnant women to determine a drug-associated risk of adverse developmental outcomes. Animal reproduction studies have not been conducted with Sterile Water for Irrigation.

All pregnancies have a background risk of birth defect, loss, or other adverse outcomes. In the U.S. general population, the estimated background risk of major birth defects and miscarriage in clinically recognized pregnancies is 2 to 4% and 15 to 20% respectively.

8.2 Lactation

Risk Summary

Appropriate administration of Sterile Water for Irrigation is not expected to cause harm to a breastfed infant. There are no data on the presence of Sterile Water for Irrigation in either human or animal milk, the effects on the breastfed infant or the effects on milk production. The lack of clinical data during lactation precludes a clear determination of the risk of Sterile Water for Irrigation to a breastfed infant; therefore, the developmental and health benefits of breastfeeding should be considered along with the mother’s clinical need for Sterile Water for Irrigation and any potential adverse effects on the breastfed infant from Sterile Water for Irrigation or from the underlying maternal condition.

8.4 Pediatric Use

Safety and effectiveness in pediatric patients have not been established. Pediatric patients are at higher risk compared to adults for developing encephalopathy as a complication of hyponatremia, if there is excessive absorption of Sterile Water for Irrigation [see Warnings and Precautions (5.2)].

8.5 Geriatric Use

Sterile Water for Irrigation should be used cautiously in older patients. Geriatric patients are more likely to have decreased cardiac, renal, or hepatic function, and other diseases or concomitant drug therapy.

10 OVERDOSAGE

Excessive rate, volume, pressure or duration of irrigation with hypotonic fluid can result in excessive fluid absorption and permanent morbidity or death as a result of hyponatremia, hypoosmolality and/or fluid overload. In the event of clinically relevant absorption of Sterile Water for Irrigation, immediate intervention may be required [see Warnings and Precautions (5.2)].

11 DESCRIPTION

Sterile Water for Irrigation contains water that is sterilized and packaged for use as an irrigant. No antimicrobial agent or other substance has been added. The pH is 5.5 (5.0 to 7.0). Sterile Water for Irrigation is hypotonic with an osmolarity of zero mOsmol/L.

The flexible plastic container is fabricated from a specially formulated polyvinyl chloride. The amount of water that can permeate from inside the container into the overwrap is insufficient to affect the fluid significantly. Water in contact with the plastic container may leach out certain chemical components from the plastic in very small amounts; however, biological testing was supportive of the safety of the plastic container materials.

The plastic pour bottle is fabricated from specially formulated polyolefin. The polyolefin is a copolymer of ethylene and propylene. The container requires no vapor barrier.

16 HOW SUPPLIED/STORAGE AND HANDLING

Sterile Water for Irrigation is supplied in single-dose plastic pour bottles and flexible plastic containers as follows:

Container | Product Codes | Fill Volume (mL) | NDC
Plastic Pour Bottle | 2F7112 | 250 | 0338-0004-02
Plastic Pour Bottle | 2F7113 | 500 | 0338-0004-03
Plastic Pour Bottle | 2F7114 | 1000 | 0338-0004-04
Plastic Pour Bottle | 2F7115 | 1500 | 0338-0004-05
Flexible Plastic Container | 2B7114 | 1000 | 0338-0003-44
Flexible Plastic Container | 2B7116 | 2000 | 0338-0003-46
Flexible Plastic Container | 2B7117 | 3000 | 0338-0003-47

Storage

Exposure of pharmaceutical products to heat should be minimized. Avoid excessive heat.

Store at room temperature (25°C): brief exposure up to 40°C does not adversely affect the product.

17 PATIENT COUNSELING INFORMATION

Inform patients, caregivers, or home healthcare providers of the following risks of Sterile Water for Irrigation:

- Hypotonicity [see Warnings and Precautions (5.1)]
- Excessive Water Absorption [see Warnings and Precautions (5.2)]

Baxter Healthcare Corporation
Deerfield, IL 60015 USA

Printed in USA
07-19-77-916

Baxter is a registered trademark of Baxter International Inc.

PACKAGE/LABEL PRINCIPAL DISPLAY PANEL

Container Label

2F7114
NDC 0338-0004-04

1000 mL

Baxter Logo

Not for Injection

For Irrigation Only

Sterile Water for
Irrigation USP

Prepared by distillation. No antimicrobial agent
or other substance has been added. pH 5.5 (5.0
to 7.0). Osmolarity 0 mOsmol/L (calc.). Sterile,
nonpyrogenic. Pour Bottle. Warning: This
solution is not isotonic and is hemolytic. Dosage
and Administration: As directed by a physician.
Cautions: Warm in oven to not more than 50ºC for
a maximum of 60 days. Discard after 60 days of
warming. Do not use unless solution is clear and
seal is intact. Discard unused portion.
Rx only. Recommended storage: Room
temperature (25ºC). Avoid excessive heat.

PL 325 Plastic

Baxter Healthcare Corporation
Deerfield, IL 60015 USA
Made in USA

LOT
EXP

FPO
(91)0709000246
Bar Code

07-09-00-0246

Bar Code Position Only*
303380004041

LOT
EXP
2000 mL
NOT FOR INJECTION
2B7116
NDC 0338-0003-46
STERILE WATER
For Irrigation USP

For irrigation only Prepared by distillation
No antimicrobial agent or other substance has been added
pH 5.5 (5.0 TO 7.0). Osmolarity 0 mOsmol/L (calc) Sterile
Nonpyrogenic Single dose container

Do not use unless fluid is clear Discard unused portion

Cautions This fluid is not isotonic and is hemolytic
Squeeze and inspect inner bag which maintains product
sterility Discard if leaks are found Rx Only Store unit in
moisture barrier overwrap at room temperature (25ºC) until
Ready to use Avoid excessive heat See insert

Sterile Water
H20
For Irrigation USP

UROMATIC container

Baxter Logo
Baxter Healthcare Corporation
Deerfield IL 60015 USA

Made in USA

PL 146 Plastic

Baxter UROMATIC and
PL 146 are trademarks of
Baxter International Inc

For product information
1-800-933-0303

1800
1600
1400
1200
1000
800
600
400
200